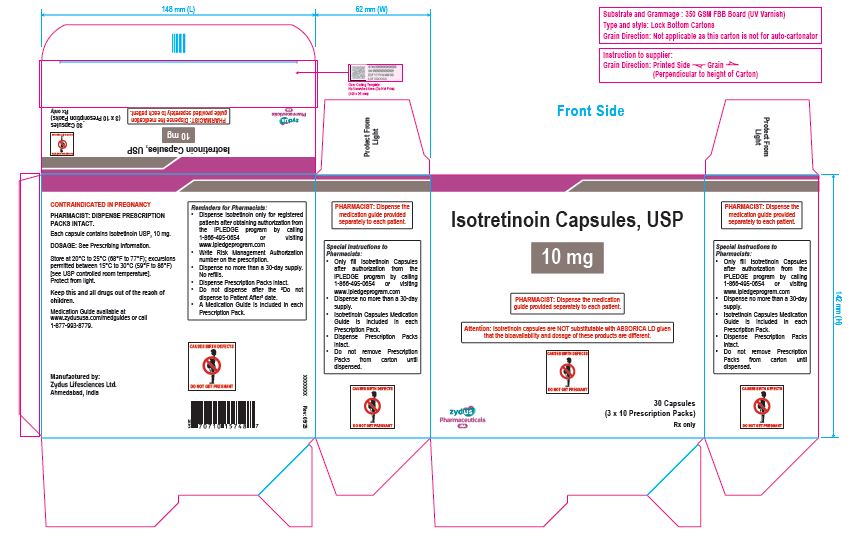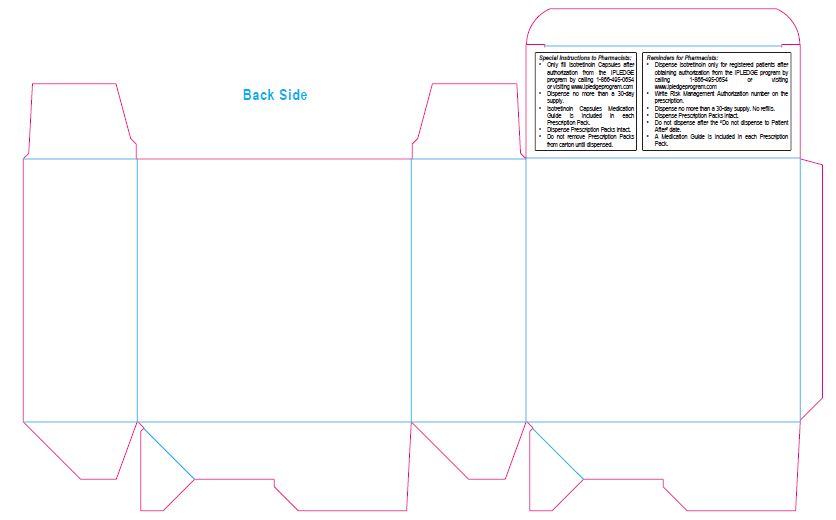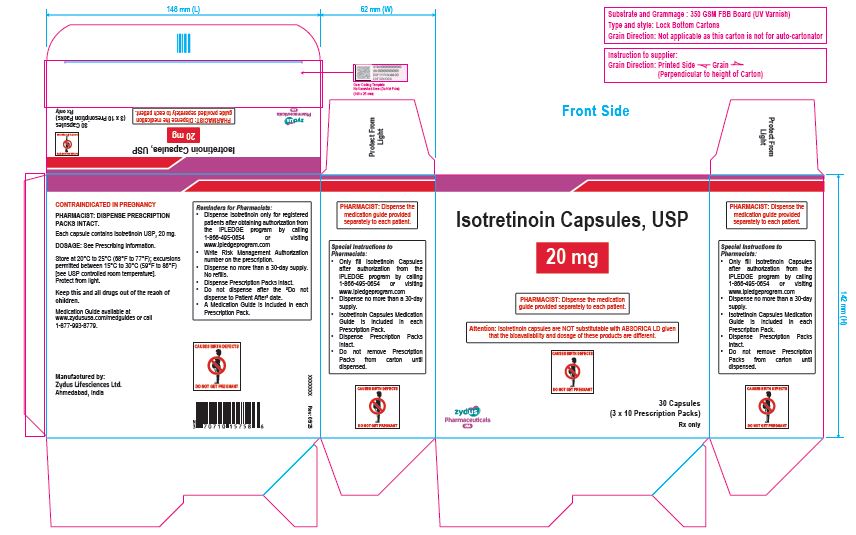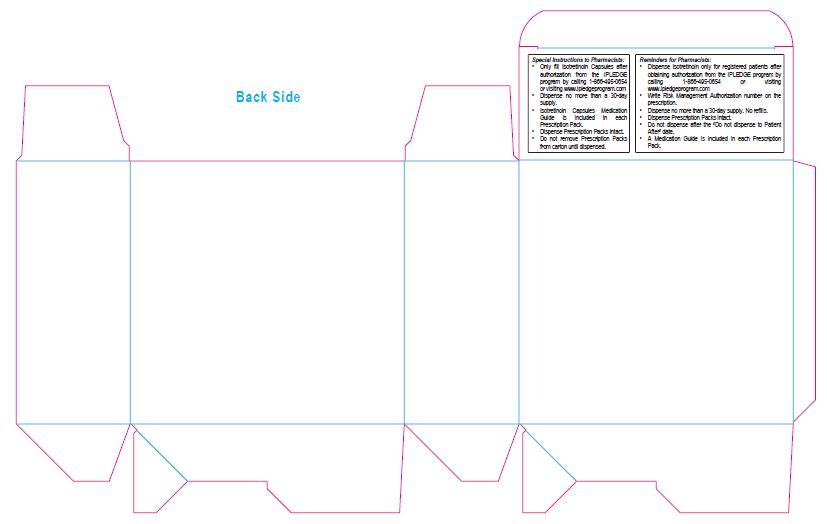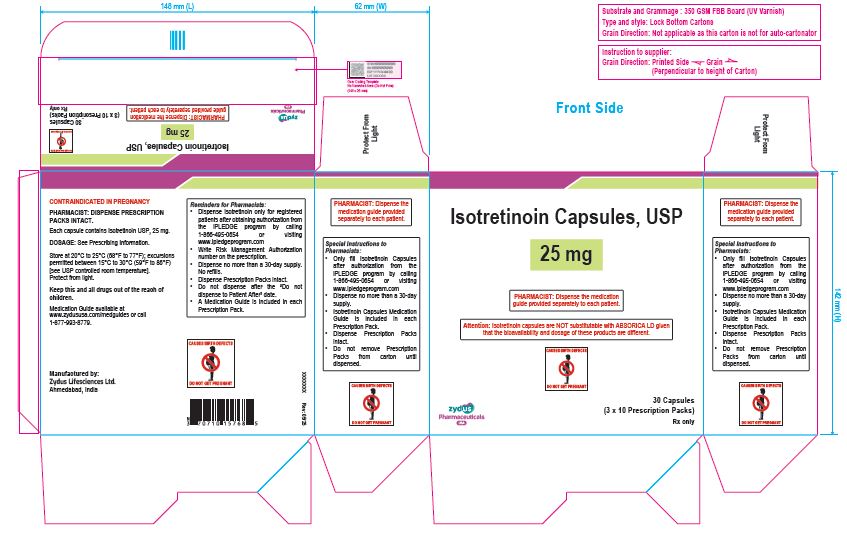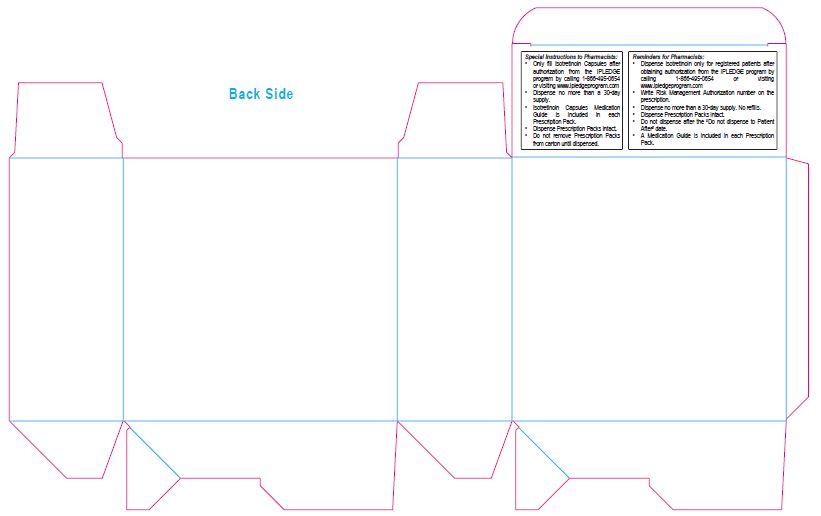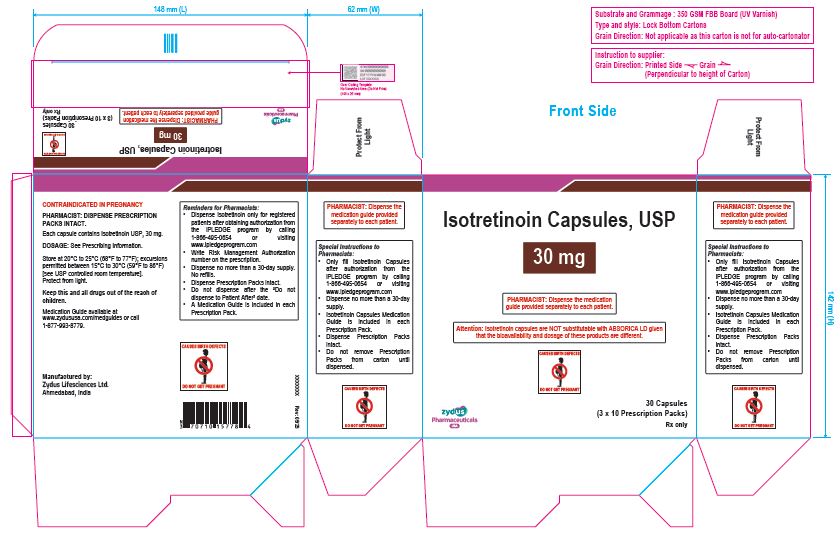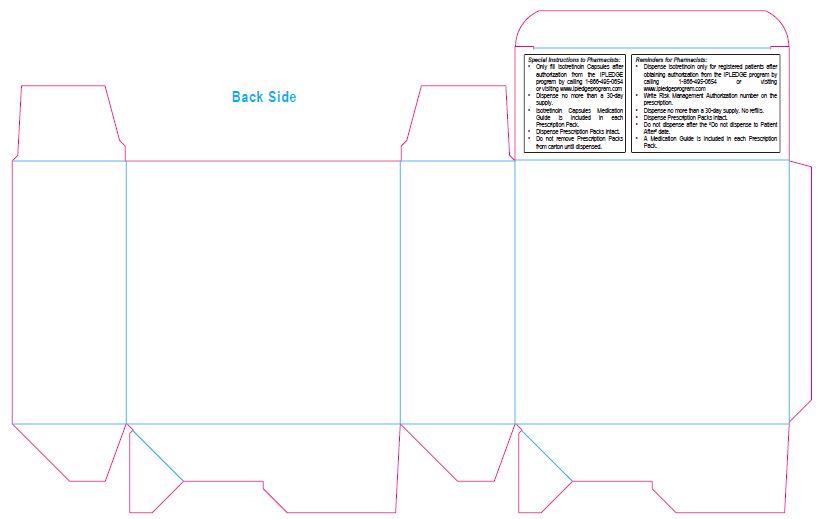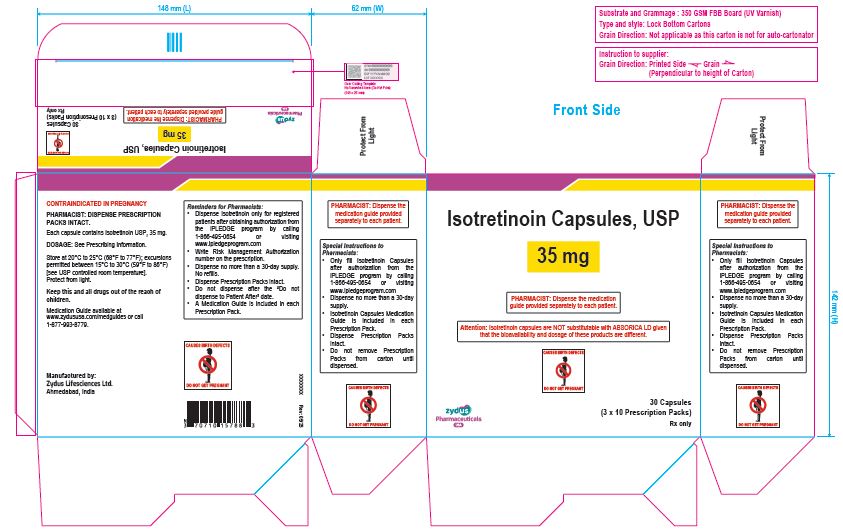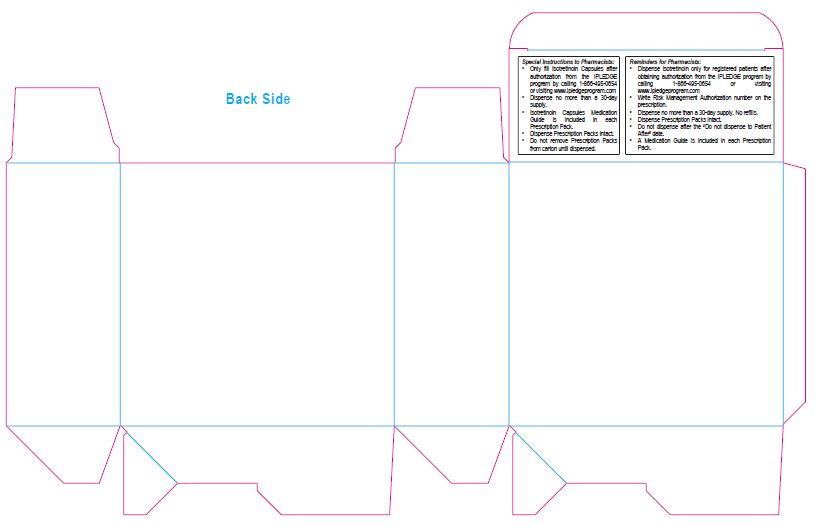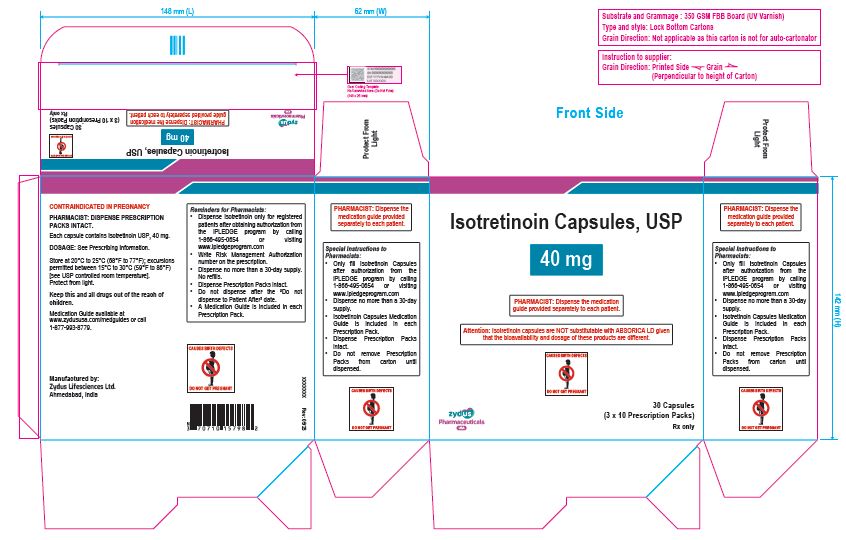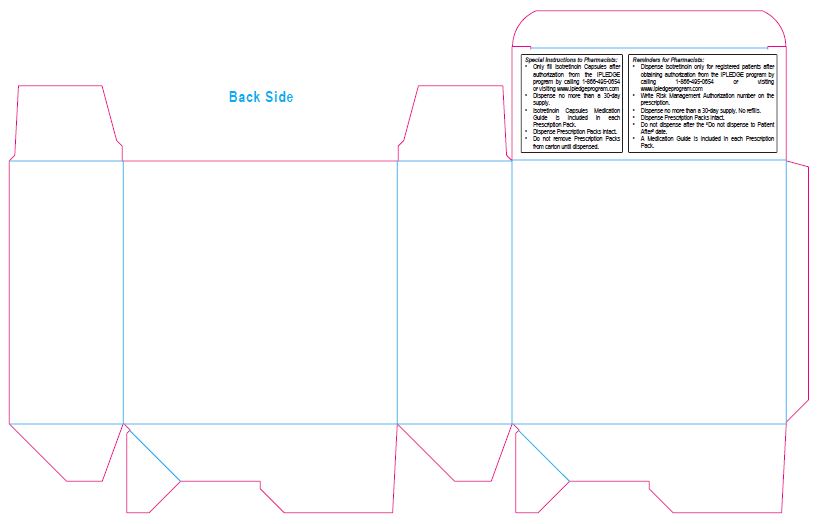 DRUG LABEL: Isotretinoin
NDC: 70771-1662 | Form: CAPSULE
Manufacturer: Zydus Lifesciences Limited
Category: prescription | Type: HUMAN PRESCRIPTION DRUG LABEL
Date: 20250604

ACTIVE INGREDIENTS: ISOTRETINOIN 10 mg/1 1
INACTIVE INGREDIENTS: FERRIC OXIDE YELLOW; FERROSOFERRIC OXIDE; GELATIN; PEG-32 HYDROGENATED PALM GLYCERIDES; POTASSIUM HYDROXIDE; PROPYL GALLATE; PROPYLENE GLYCOL; SHELLAC; SORBITAN MONOOLEATE; SOYBEAN OIL; TITANIUM DIOXIDE; WATER

PACKAGE LABEL.PRINCIPAL DISPLAY PANEL

NDC 70771-1662-8

Isotretinoin Capsules USP, 10 mg

30 Capsules

Rx only

NDC 70771-1663-8

Isotretinoin Capsules USP, 20 mg

30 Capsules

Rx only

NDC 70771-1664-8

Isotretinoin Capsules USP, 25 mg

30 Capsules

Rx only

NDC 70771-1665-8

Isotretinoin Capsules USP, 30 mg

30 Capsules

Rx only

NDC 70771-1666-8

Isotretinoin Capsules USP, 35 mg

30 Capsules

Rx only

NDC 70771-1667-8

Isotretinoin Capsules USP, 40 mg

30 Capsules

Rx only